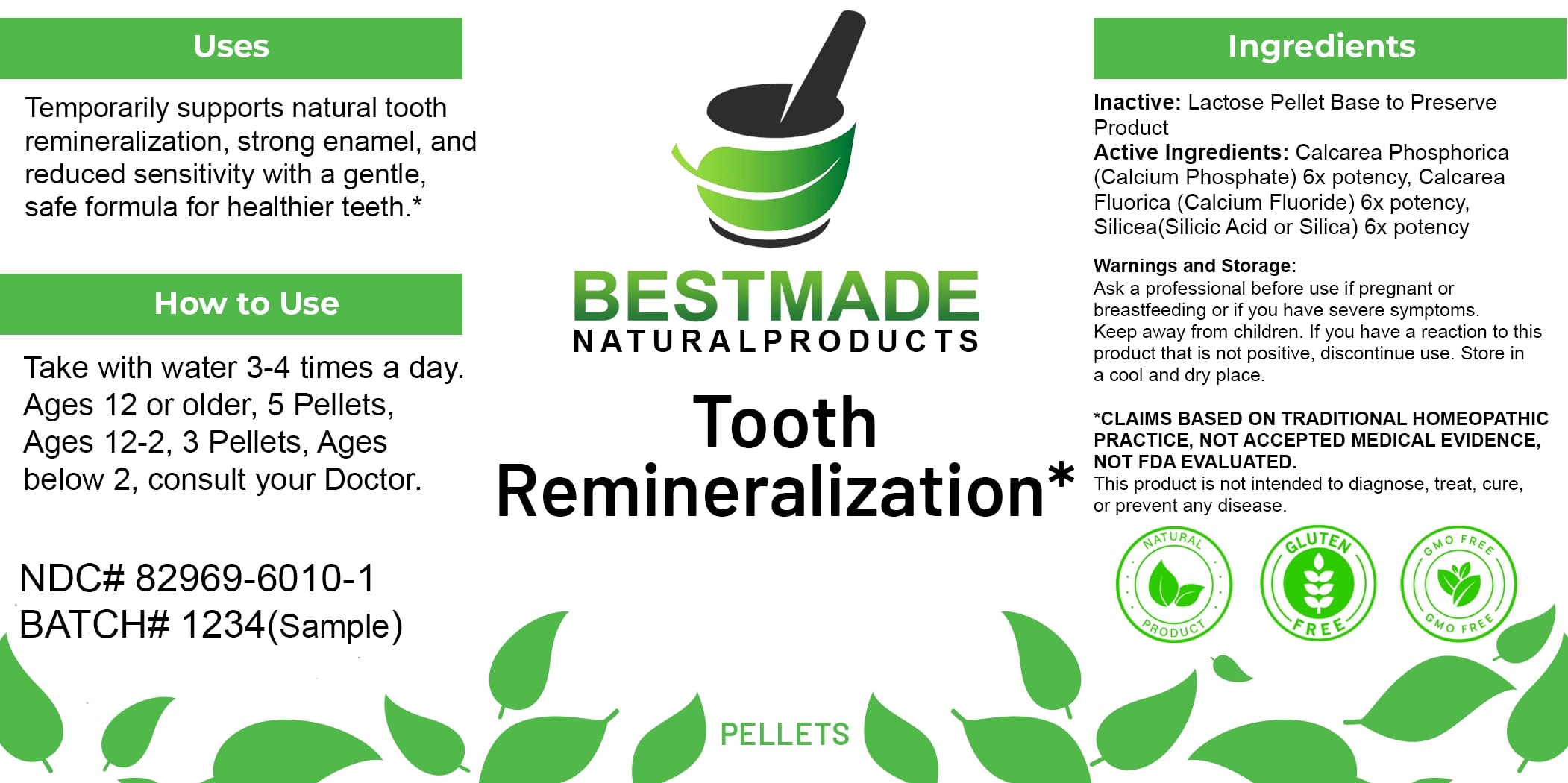 DRUG LABEL: Bestmade Natural Products Tooth Remineralization Remedy
NDC: 82969-6010 | Form: TABLET, SOLUBLE
Manufacturer: Bestmade Natural Products
Category: homeopathic | Type: HUMAN OTC DRUG LABEL
Date: 20250314

ACTIVE INGREDIENTS: TRIBASIC CALCIUM PHOSPHATE 6 [hp_X]/6 [hp_X]; CALCIUM FLUORIDE 6 [hp_X]/6 [hp_X]; SILICA 6 [hp_X]/6 [hp_X]
INACTIVE INGREDIENTS: LACTOSE 6 [hp_X]/6 [hp_X]; SUCROSE 6 [hp_X]/6 [hp_X]

Tooth Remineralization Remedy

DOSAGE AND ADMINISTRATION

How to Use

Take with water 3-4 times a day. Ages 12 or older, 5 Pellets, Ages 12-2, 3 Pellets, Ages below 2, consult your Doctor.

INACTIVE INGREDIENT

Ingredients

Inactive: Lactose Pellet Base to Preserve Product

ACTIVE INGREDIENT

Active Ingredients: Calcarea Phosphorica (Calcium Phosphate) 6x potency, Calcarea Fluorica (Calcium Fluoride) 6x potency, Silicea (Silicic Acid or Silica) 6x potency

KEEP OUT OF REACH OF CHILDREN

Warnings and Storage:

Ask a professional before use if pregnant or breastfeeding or if you have severe symptoms. Keep away from children. If you have a reaction to this product that is not positive, discontinue use. Store in a cool and dry place.

Warnings and Storage:

Ask a professional before use if pregnant or breastfeeding or if you have severe symptoms. Keep away from children. If you have a reaction to this product that is not positive, discontinue use. Store in a cool and dry place.

*CLAIMS BASED ON TRADITIONAL HOMEOPATHIC PRACTICE, NOT ACCEPTED MEDICAL EVIDENCE, NOT FDA EVALUATED. This product is not intended to diagnose, treat, cure, or prevent any disease.

Uses

Temporarily supports natural tooth remineralization, strong enamel, and reduced sensitivity with a gentle, safe formula for healthier teeth.*

*CLAIMS BASED ON TRADITIONAL HOMEOPATHIC PRACTICE, NOT ACCEPTED MEDICAL EVIDENCE, NOT FDA EVALUATED. This product is not intended to diagnose, treat, cure, or prevent any disease.

Uses

Temporarily supports natural tooth remineralization, strong enamel, and reduced sensitivity with a gentle, safe formula for healthier teeth.*

*CLAIMS BASED ON TRADITIONAL HOMEOPATHIC PRACTICE, NOT ACCEPTED MEDICAL EVIDENCE, NOT FDA EVALUATED. This product is not intended to diagnose, treat, cure, or prevent any disease.

Entire package label